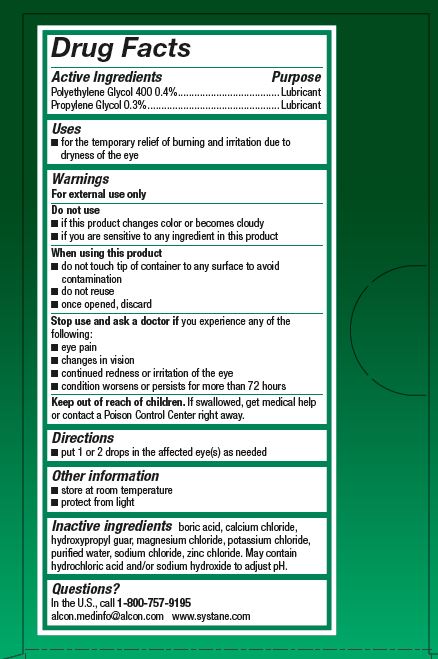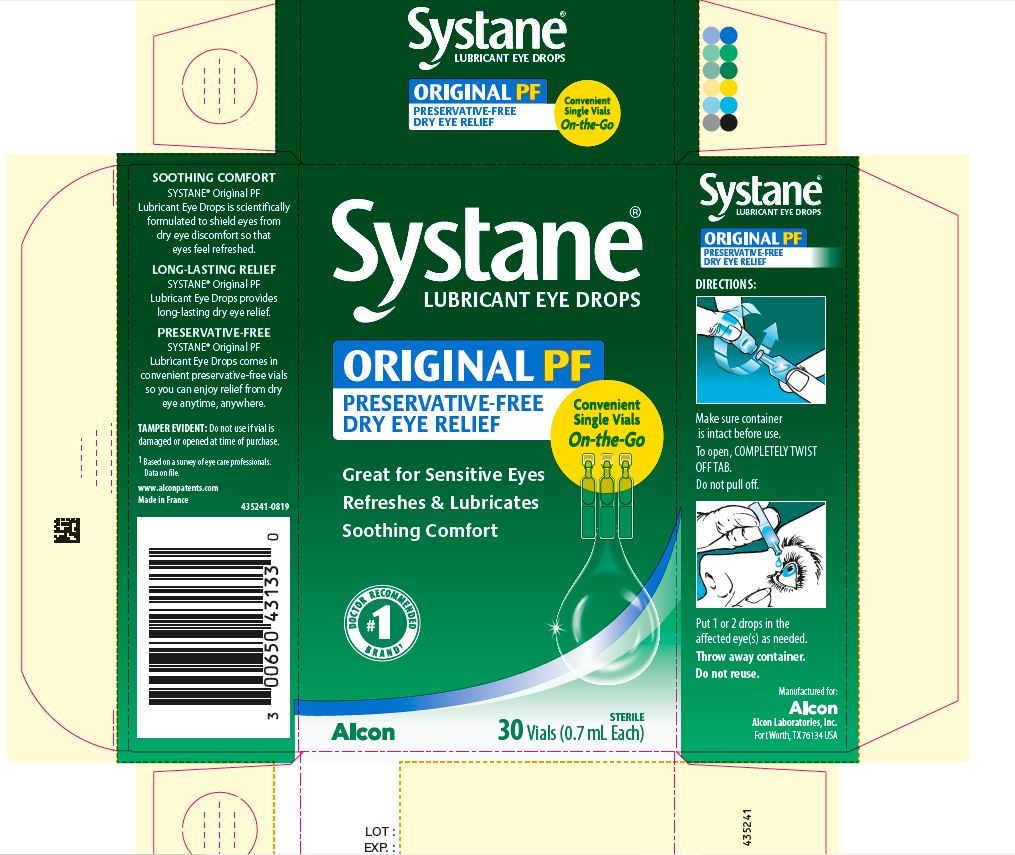 DRUG LABEL: Systane
NDC: 0065-0431 | Form: SOLUTION/ DROPS
Manufacturer: Alcon Research Ltd
Category: otc | Type: HUMAN OTC DRUG LABEL
Date: 20231215

ACTIVE INGREDIENTS: Polyethylene Glycol 400 4 mg/1 mL; PROPYLENE GLYCOL 3 mg/1 mL
INACTIVE INGREDIENTS: BORIC ACID; CALCIUM CHLORIDE; GUAR GUM; MAGNESIUM CHLORIDE; POTASSIUM CHLORIDE; WATER; SODIUM CHLORIDE; ZINC CHLORIDE; HYDROCHLORIC ACID; SODIUM HYDROXIDE

Systane
Lubricant Eye Drops

Active Ingredients | Purpose
Polyethylene Glycol 400 0.4% | Lubricant
Propylene Glycol 0.3% | Lubricant

Uses

- For the temporary relief of burning and irritation due to dryness of the eye

Warnings

For external use only

Do not use

- if this product changes color or becomes cloudy
- if you are sensitive to any ingredient in this product

When using this product

- do not touch tip of container to any surface to avoid contamination
- do not reuse
- once opened, discard

Stop use and ask a doctor if you experience any of the following:

- eye pain
- changes in vision
- continued redness or irritation of the eye
- condition worsens or persists for more than 72 hours

Keep out of reach of children.

If swallowed, get medical help or contact a Poison Control Center right away.

Directions

- instill 1 or 2 drops in the affected eye(s) as needed

Other Information

- store at room temperature
- protect from light

Inactive Ingredients

boric acid, calcium chloride, hydroxypropyl guar, magnesium chloride, potassium chloride, purified water, sodium chloride, zinc chloride. May contain hydrochloric acid and/or sodium hydroxide to adjust pH.

Questions?

In the U.S. call 1-800-757-9195
alcon.medinfo@alcon.com
www.systane.com

Principal Display Panel

Systane®
LUBRICANT EYE DROPS
ORIGINAL PF
PRESERVATIVE-FREE
DRY EYE RELIEF
Convenient
Single Vials
On-the-Go
Great for Sensitive Eyes
Refreshes & Lubricates
Soothing Comfort
#1 Doctor Recommended Brand^1
STERILE
30 Vials 0.7 mL Each
Alcon

Side Panel (s)

SOOTHING COMFORT
SYSTANE® Original PF
Lubricant Eye Drops is scientifically
formulated to shield eyes from
dry eye discomfort so that
eyes feel refreshed.
LONG-LASTING RELIEF
SYSTANE® Original PF
Lubricant Eye Drops provides
long-lasting dry eye relief.
PRESERVATIVE-FREE
SYSTANE® Original PF
Lubricant Eye Drops comes in
convenient preservative-free vials
so you can enjoy relief from dry
eye anytime, anywhere.
TAMPER EVIDENT: Do not use if vial is
damaged or opened at time of purchase.
^1 Based on a survey of eye care professionals.
Data on file.
www.alconpatents.com
Made in France
435241-0819

Systane®
LUBRICANT EYE DROPS
ORIGINAL PF
PRESERVATIVE-FREE
DRY EYE RELIEF
DIRECTIONS:
Make sure container
is intact before use.
To open, COMPLETELY TWIST
OFF TAB.
Do not pull off.
Put 1 or 2 drops in the
affected eye(s) as needed.
Throw away container.
Do not reuse.

Manufactured for:
ALCON
Alcon Laboratories, Inc.
Fort Worth, TX 76134 USA